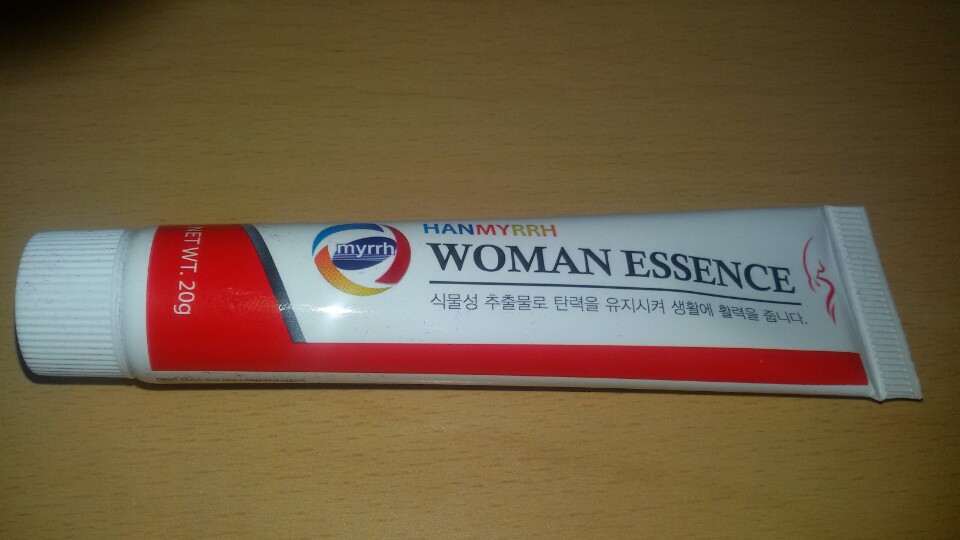 DRUG LABEL: MYRRH WOMAN ESSENCE
NDC: 72263-0001 | Form: LIQUID
Manufacturer: MIR BIOTECHNOLOGY
Category: otc | Type: HUMAN OTC DRUG LABEL
Date: 20180426

ACTIVE INGREDIENTS: ALCOHOL 5 g/100 g
INACTIVE INGREDIENTS: WATER; MENTHOL

ACTIVE INGREDIENT

alcohol

INACTIVE INGREDIENT

water, menthol, citric acid, etc

PURPOSE

Cold odor Trichomonas candida infection treatment

Lack of come secretion

Vaginal cold urinary incontinence

Insensitivity to orgasms

Dry, rub and scar of Y zone

Lack of vaginal elasticity

Menopausal hormone imbalance

Lack of libido

WARNINGS

1. If the following symptoms occur after product use, stop using the product immediately and consult a dermatologist (continuous use can exacerbate the symptoms).
1) Occurrence of red spots, swelling, itchiness, and other irritation
2) If the symptoms above occur after the application area is exposed to direct sunlight

2. Do not use on open wounds, eczema, and other irritations
3. Precaution for Storage and Handling
1) Close the lid after use
2) Keep out of reach of infants and children
3) Do not to store in a place with high/low temperature and exposed to direct sunlight

4. Use as avoiding eye areas.

Keep out of reach of children.

INDICATIONS AND USAGE

Wash the Y zone thoroughly, then put the Woman Essence in a pill and put it deeply into the vagina
After 7 days, it is steadily used for 2 ~ 3 days for 4 months.

DOSAGE AND ADMINISTRATION

for vaginal use only